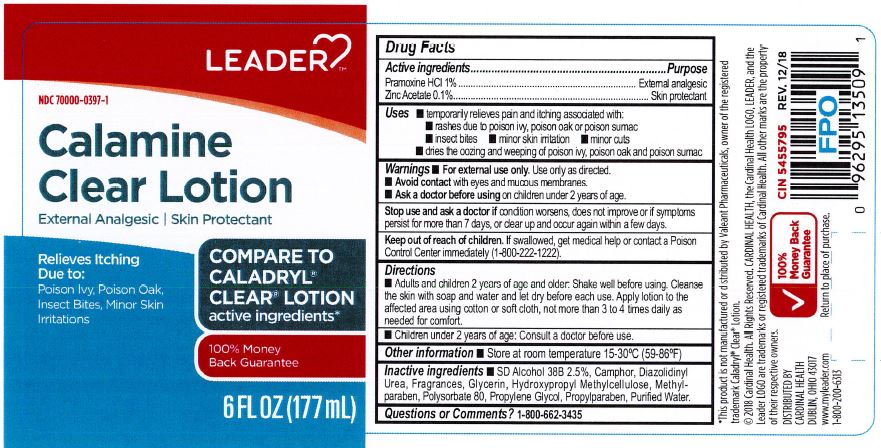 DRUG LABEL: Calamine Clear
NDC: 70000-0397 | Form: LOTION
Manufacturer: Cardinal Health, 110 dba Leader
Category: otc | Type: HUMAN OTC DRUG LABEL
Date: 20240513

ACTIVE INGREDIENTS: PRAMOXINE HYDROCHLORIDE 10 mg/1 mL; ZINC ACETATE 1 mg/1 mL
INACTIVE INGREDIENTS: DIAZOLIDINYL UREA; POLYSORBATE 80; CAMPHOR (NATURAL); ALCOHOL; GLYCERIN; HYPROMELLOSE, UNSPECIFIED; METHYLPARABEN; PROPYLENE GLYCOL; WATER; PROPYLPARABEN

Leader Calamine Clear

ACTIVE INGREDIENT

Pramoxine HCl 1%

Zinc Acetate 0.1%

PURPOSE

External Analgesic & Skin Protectant

INDICATIONS AND USAGE

Temporarily Relieves Pain and Itching Associated with:

rashes due to poison ivy, poison oak, or poison sumac
insect bites
minor skin irritation
minor cuts
dries the oozing and weeping of poison ivy, poison oak and poison sumac

WARNINGS

For external use only. Use only as directed.

Acoid contact with eyes and mucous membranes

Ask a doctor before using on children under 2 years of age.

Keep out of reach of children. If swallowed, get medical help or contact a Poison Control Center immediately (1-800-222-1222)

DOSAGE AND ADMINISTRATION

Adults and children 2 years of age and older: Shake well before using. Cleanse the skin with soap and water and let dry before each use. Apply lotion fo the affected area using cotton or soft cloth, not more than 3 to 4 times dialy as needed for comfort.

INACTIVE INGREDIENT

SD Alcohol 38B 2.5%

Camphor

Diazolidinyl Usea

Fragrances

Glycerin

Hydroxypropyl Methylcellulose

Methylparaben

Polysorbate 80

Propylene Glycol

Propylparaben

Purified Water